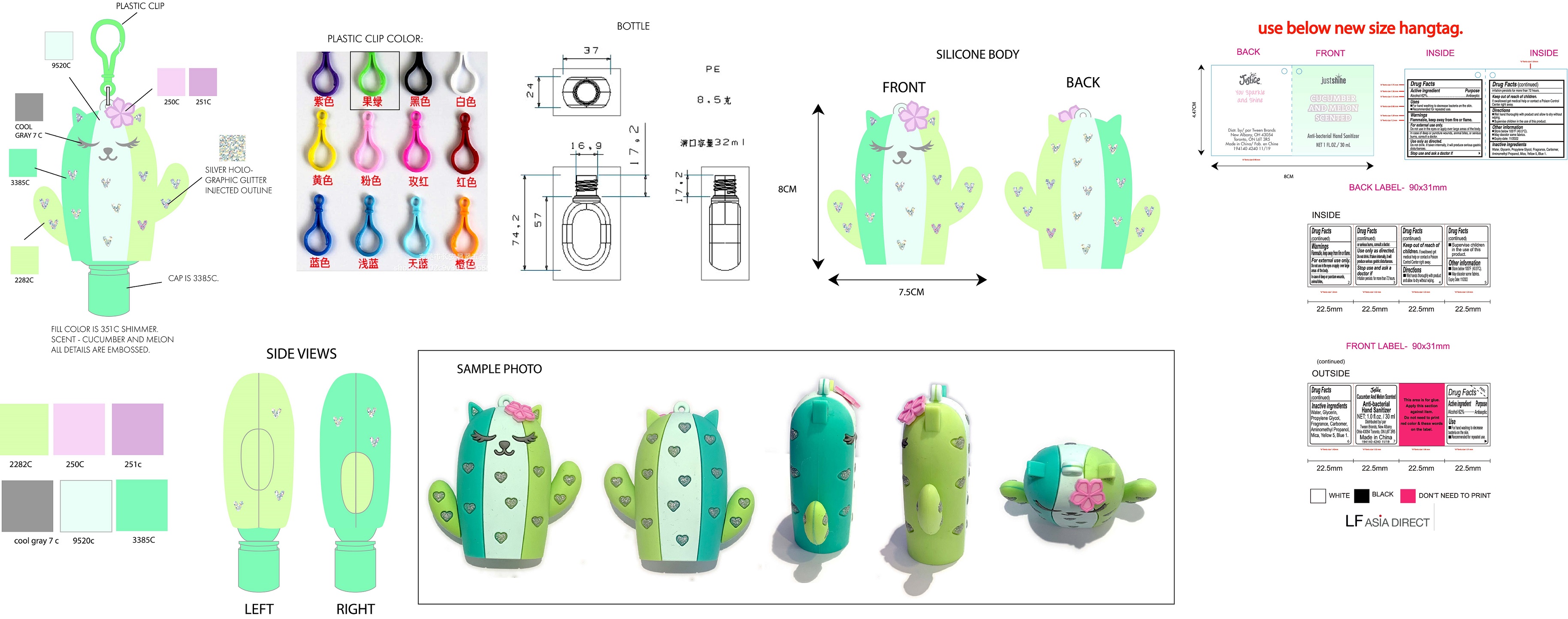 DRUG LABEL: Justice Cucumber And Melon Scented Anti-bacterial Hand Sanitizer
NDC: 60637-140 | Form: GEL
Manufacturer: Tween Brands, Inc.
Category: otc | Type: HUMAN OTC DRUG LABEL
Date: 20231103

ACTIVE INGREDIENTS: ALCOHOL 620 mg/1 mL
INACTIVE INGREDIENTS: WATER; GLYCERIN; PROPYLENE GLYCOL; CARBOMER HOMOPOLYMER, UNSPECIFIED TYPE; AMINOMETHYLPROPANOL; MICA; FD&C YELLOW NO. 5; FD&C BLUE NO. 1

Justice Cucumber And Melon Scented Anti-bacterial Hand Sanitizer

Active ingredient

Alcohol 62%

Purpose

Antiseptic

Use

- for hand-washing to decrease bacteria on the skin,
- Recommended for repeated area

Warnings

Flammable, keep away from fire or flames

For external use only

Do not use

in the eyes or apply over large areas of the body. In case of deep or puncture wounds, animals bites, or serious burns, consult a doctor. Use only as directed. Do not drink. If taken internally, it will produce serious gastric disturbances.

Stop use and ask a doctor if

- Irritation persists for more than 72 hours.

Keep out of reach of children.

if swallowed get medical help or contact a Poison Control Center right away.

Directions

- wet hands thoroughly with product and allow to dry without wiping
- Supervise children in the use of this product.

Inactive ingredients

Water, Glycerin, Propylene Glycol, Fragrance, Carbomer, Aminomethyl Propanol, Mica, Yellow 5, Blue 1.

Other information

- Store below 105°F (40.5°C).
- May discolor some fabrics: Expiry Date 11/2022